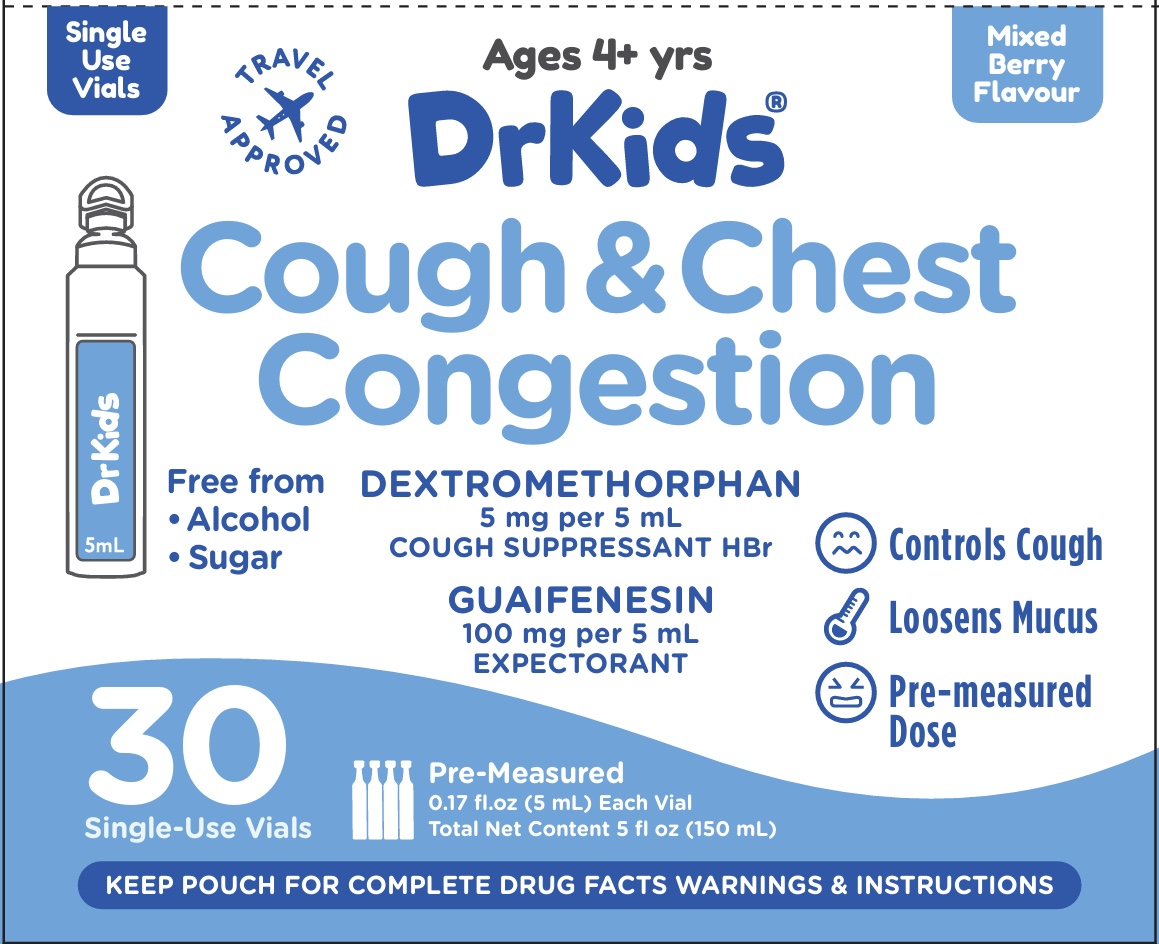 DRUG LABEL: Dr Kids
NDC: 73282-2523 | Form: SOLUTION
Manufacturer: CalmCo LLC
Category: otc | Type: HUMAN OTC DRUG LABEL
Date: 20251002

ACTIVE INGREDIENTS: GUAIFENESIN 100 mg/5 mL; DEXTROMETHORPHAN HYDROBROMIDE 5 mg/5 mL
INACTIVE INGREDIENTS: ANHYDROUS CITRIC ACID; SORBITOL; SODIUM BENZOATE; WATER; PROPYLENE GLYCOL; SUCRALOSE; CARBOXYMETHYLCELLULOSE; SACCHARIN SODIUM

DrKids Children's Cough and Chest Congestion (A)

Drug Facts

.

Active Ingredient and Purpose

.

Active ingredient (in each 5 mL vial) | Purpose
Dextromethorphan HBr 5mg.............. | Cough supressant
Guaifenesin 100mg............ | Expectorant

Uses

- temporarily relieves cough due to minor bronchial irritation associated with a cold
- helps loosen phlegm (mucus) and thin bronchial secretions to make coughs more productive

Warnings

Do not use

- if your child is now taking a prescription monoamine oxidase inhibitor (MAOI) (certain drugs for depression, psychiatric, or emotional conditions, or Parkinson’s disease), or for two weeks after stopping the MAOI drug. If you do not know if your child’s prescription drug contains an MAOI, ask a doctor or pharmacist before giving this product

Ask a doctor before use if your child has

- a persistent or chronic cough such as occurs with asthma, or emphysema, or if cough is accompanied by excessive phlegm (mucus)

Stop use and ask a doctor if your child has

- a cough that persists for more than 1 week, tends to recur, or is accompanied by fever, rash, or persistent headache. A persistent cough may be a sign of a serious condition

Keep out of reach of children.

In case of accidental overdose, get medical help or contact a Poison Control Center right away (1-800-222-1222).

Directions

- this product does not contain directions or complete warnings for adult use
- do not exceed 6 doses in a 24-hour period
- follow the “Easy to Use” instructions on the pouch
- use the dose that corresponds to your child’s age
- discard unused portion

Age (Years) | Dose
Under 4 | consult a doctor
4 to under 6 | 1 vial every 4 hours
6 to under 12 | 1-2 vials every 4 hours
12 and older | 2-4 vials every 4 hours

Other information

- each 5 mL vial contains: sodium 7 mg
- store between 68-77°F (20-25°C)
- do not use if pouch or vial is punctured, torn or open

Inactive ingredients

anhydrous citric acid, carboxymethylcellulose, flavor, propylene glycol, sodium benzoate, saccharin sodium, sorbitol, sucralose, water

Questions or comments?

+1-941-202-3270 (M-F) 9AM-5PM EST or visit www.DrKids.com

Distributed by: CalmCo LLC, Sarasota, FL 34240

Made in Dominican Republic